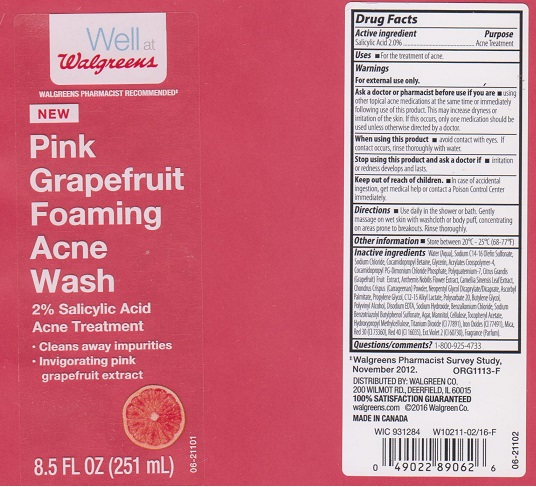 DRUG LABEL: WELL AT WALGREENS
NDC: 0363-0829 | Form: LIQUID
Manufacturer: WALGREEN COMPANY
Category: otc | Type: HUMAN OTC DRUG LABEL
Date: 20160317

ACTIVE INGREDIENTS: SALICYLIC ACID 20 mg/1 mL
INACTIVE INGREDIENTS: WATER; SODIUM C14-16 OLEFIN SULFONATE; COCAMIDOPROPYL BETAINE; GLYCERIN; SODIUM CHLORIDE; CARBOMER COPOLYMER TYPE A (ALLYL PENTAERYTHRITOL CROSSLINKED); COCAMIDOPROPYL PG-DIMONIUM CHLORIDE PHOSPHATE; POLYQUATERNIUM-7 (70/30 ACRYLAMIDE/DADMAC; 1600000 MW); PUMMELO; CHAMAEMELUM NOBILE FLOWER; GREEN TEA LEAF; CHONDRUS CRISPUS; NEOPENTYL GLYCOL DICAPRYLATE/DICAPRATE; ASCORBYL PALMITATE; PROPYLENE GLYCOL; C12-15 ALKYL LACTATE; POLYSORBATE 20; BUTYLENE GLYCOL; POLYVINYL ALCOHOL; EDETATE DISODIUM; SODIUM HYDROXIDE; BENZALKONIUM CHLORIDE; SODIUM BENZOTRIAZOLYL BUTYLPHENOL SULFONATE; AGAR; MANNITOL; POWDERED CELLULOSE; .ALPHA.-TOCOPHEROL ACETATE; HYPROMELLOSES; TITANIUM DIOXIDE; FERRIC OXIDE RED; MICA; D&C RED NO. 30; FD&C RED NO. 40; EXT. D&C VIOLET NO. 2

DRUG FACTS

Active ingredient

Salicylic Acid 2.0%

Purpose

Acne Treatment

Uses

For the treatment of acne.

Warnings

For external use only.

Ask doctor or pharmacist before use if you are

- using other topical acne medications at the same time or immediately following use of this product. This may increase dryness or irritation of the skin. If this occurs, only one medication should be used unless otherwise directed by a doctor.

When using this product

- avoid contact with eyes. If contact occurs, rinse thoroughly with water.

Stop using this product and ask a doctor if

- irritation or redness develops and lasts.

Keep out of reach of children.

- In case of accidental ingestion, get medical help or contact a Poison Control Center immediately.

Directions

- Use daily in the shower or bath. Gently massage on wet skin with washcloth or body puff, concentrating on areas prone to breakouts. Rinse thoroughly.

Other information

- Store between 20°C-25°C (68-77°F)

Inactive ingredients

Water (Aqua), Sodium C14-16 Olefin Sulfonate, Sodium Chloride, Cocamidopropyl Betaine, Glycerin, Acrylates Crosspolymer-4, Cocamidopropyl PG-Dimonium Chloride Phosphate, Polyquaternium-7, Citrus Grandis (Grapefruit) Fruit Extract, Anthemis Nobilis Flower Extract, Camellia Sinensis Leaf Extract, Chondrus Crispus (Carrageenan) Powder, Neopentyl Glycol Dicaprylate/Dicaprate, Ascorbyl Palmitate, Propylene Glycol, C12-15 Alkyl Lactate, Polysorbate 20, Butylene Glycol, Polyvinyl Alcohol, Disodium EDTA, Sodium Hydroxide, Benzalkonium Chloride, Sodium Benzotriazolyl Butylphenol Sulfonate, Agar, Mannitol, Cellulose, Tocopheryl Acetate, Hydroxypropyl Methylcellulose, Titanium Dioxide (CI 77891), Iron Oxides (CI 77491), Mica, Red 30 (CI 73360), Red 40 (CI 16035), Ext. Violet 2 (CI 60730), Fragrance (Parfum).

Questions/comments?

1-800-925-4733